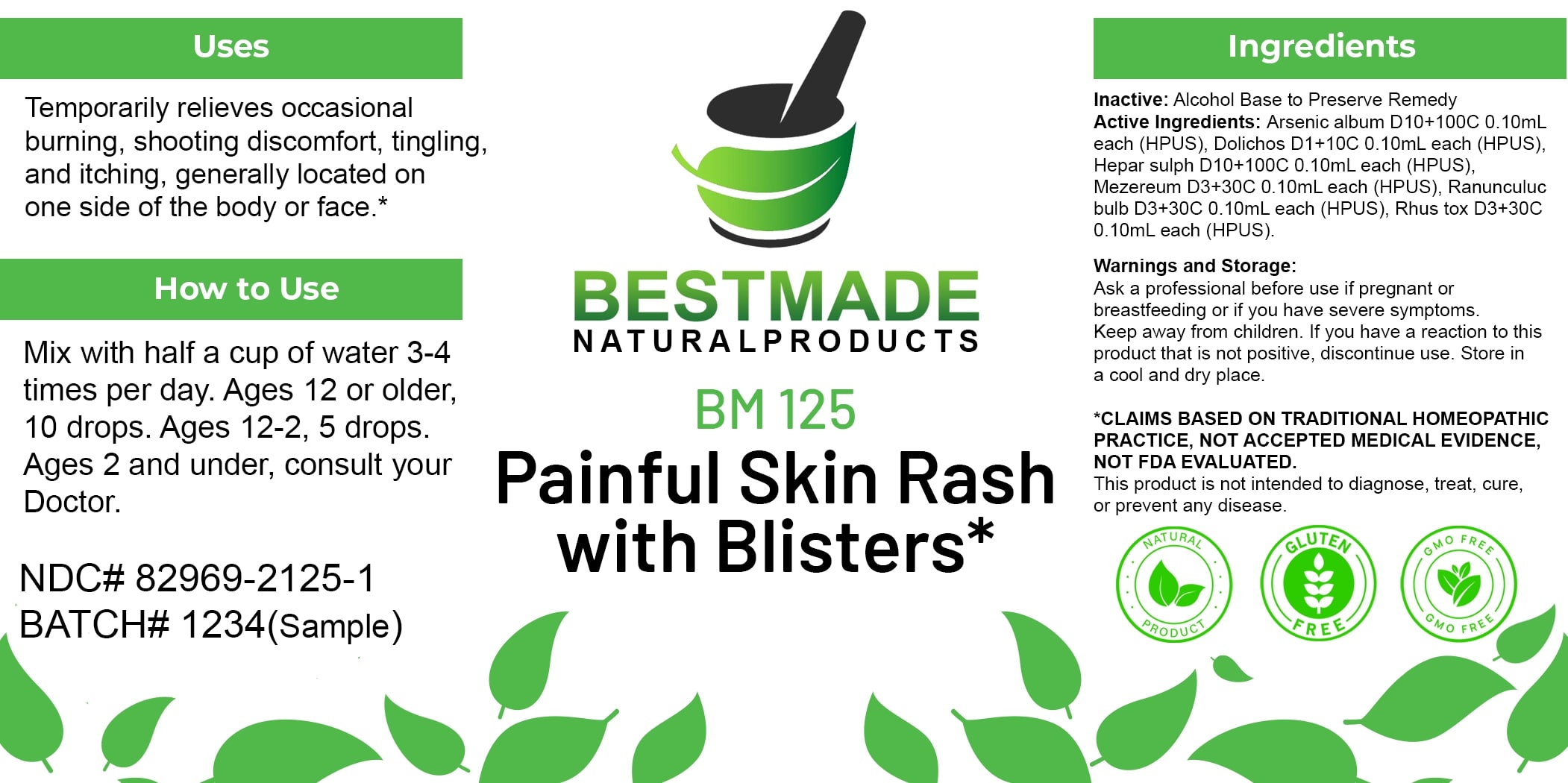 DRUG LABEL: Bestmade Natural Products BM125
NDC: 82969-2125 | Form: LIQUID
Manufacturer: Bestmade Natural Products
Category: homeopathic | Type: HUMAN OTC DRUG LABEL
Date: 20250210

ACTIVE INGREDIENTS: DAPHNE MEZEREUM BARK 30 [hp_C]/30 [hp_C]; TOXICODENDRON PUBESCENS LEAF 30 [hp_C]/30 [hp_C]; ARSENIC TRIOXIDE 30 [hp_C]/30 [hp_C]; CALCIUM SULFIDE 30 [hp_C]/30 [hp_C]; MUCUNA PRURIENS FRUIT TRICHOME 30 [hp_C]/30 [hp_C]; RANUNCULUS BULBOSUS WHOLE 30 [hp_C]/30 [hp_C]
INACTIVE INGREDIENTS: ALCOHOL 30 [hp_C]/30 [hp_C]

BM125

DOSAGE AND ADMINISTRATION

How to Use

Mix with half a cup of water 3-4 times per day. Ages 12 or older, 10 drops. Ages 12-2, 5 drops. Ages 2 and under, consult your Doctor.

Inactive:

Alcohol Base to Preserve Product

ACTIVE INGREDIENT

Active Ingredients: Arsenic album D10+100C 0.10mL each (HPUS), Dolichos D1+10C 0.10mL each (HPUS), Hepar sulph D10+100C 0.10mL each (HPUS), Mezereum D3+30C 0.10mL each (HPUS), Ranunculuc bulb D3+30C 0.10mL each (HPUS), Rhus tox D3+30C 0.10mL each (HPUS).

Uses
Temporarily relieves occasional burning, shooting discomfort, tingling, and itching, generally located on one side of the body or face.*

Uses
Temporarily relieves occasional burning, shooting discomfort, tingling, and itching, generally located on one side of the body or face.*

KEEP OUT OF REACH OF CHILDREN

Warnings and Storage:

Ask a professional before use if pregnant or breastfeeding or if you have severe symptoms.

Keep away from children. If you have a reaction to this product that is not positive, discontinue use. Store in a cool and dry place

*CLAIMS BASED ON TRADITIONAL HOMEOPATHIC PRACTICE, NOT ACCEPTED MEDICAL EVIDENCE NOT FDA EVALUATED.
This product is not intended to diagnose, treat, cure, or prevent any disease.

Warnings and Storage:

Ask a professional before use if pregnant or breastfeeding or if you have severe symptoms.

Keep away from children. If you have a reaction to this product that is not positive, discontinue use. Store in a cool and dry place

*CLAIMS BASED ON TRADITIONAL HOMEOPATHIC PRACTICE, NOT ACCEPTED MEDICAL EVIDENCE NOT FDA EVALUATED.
This product is not intended to diagnose, treat, cure, or prevent any disease.

Entire package label